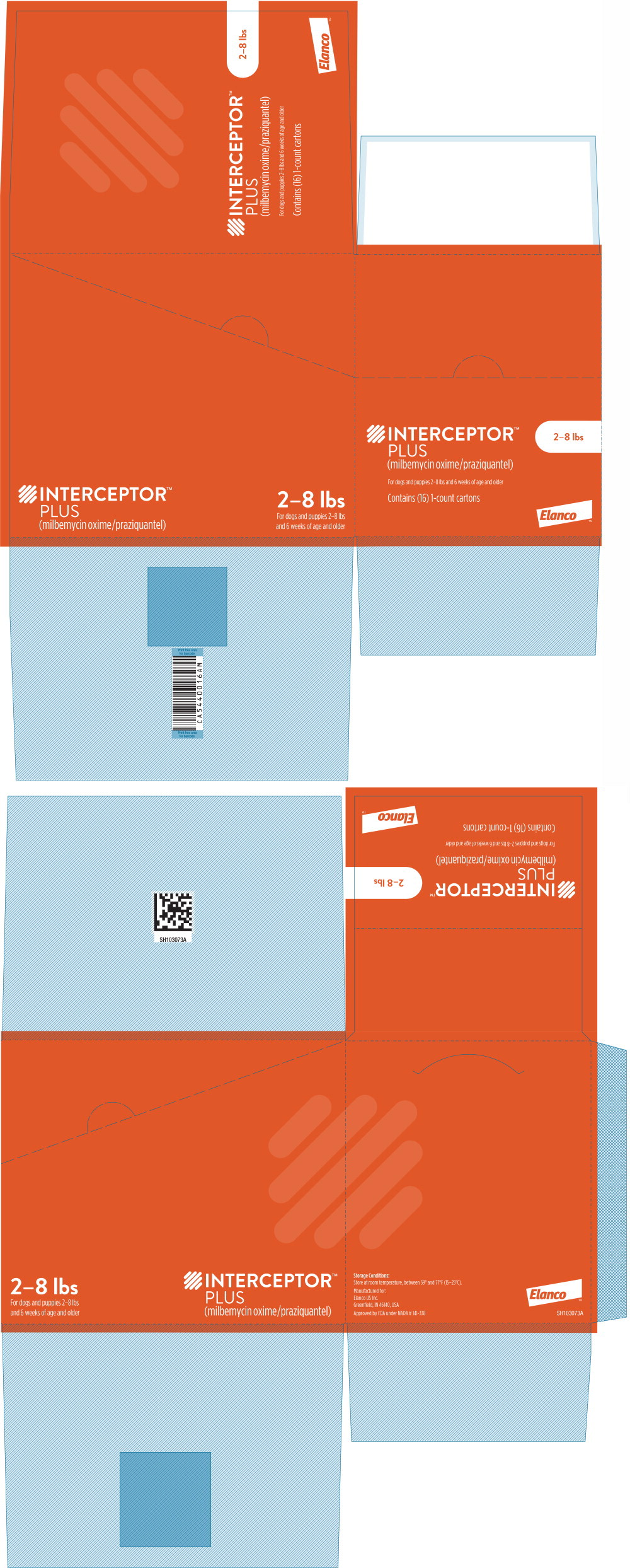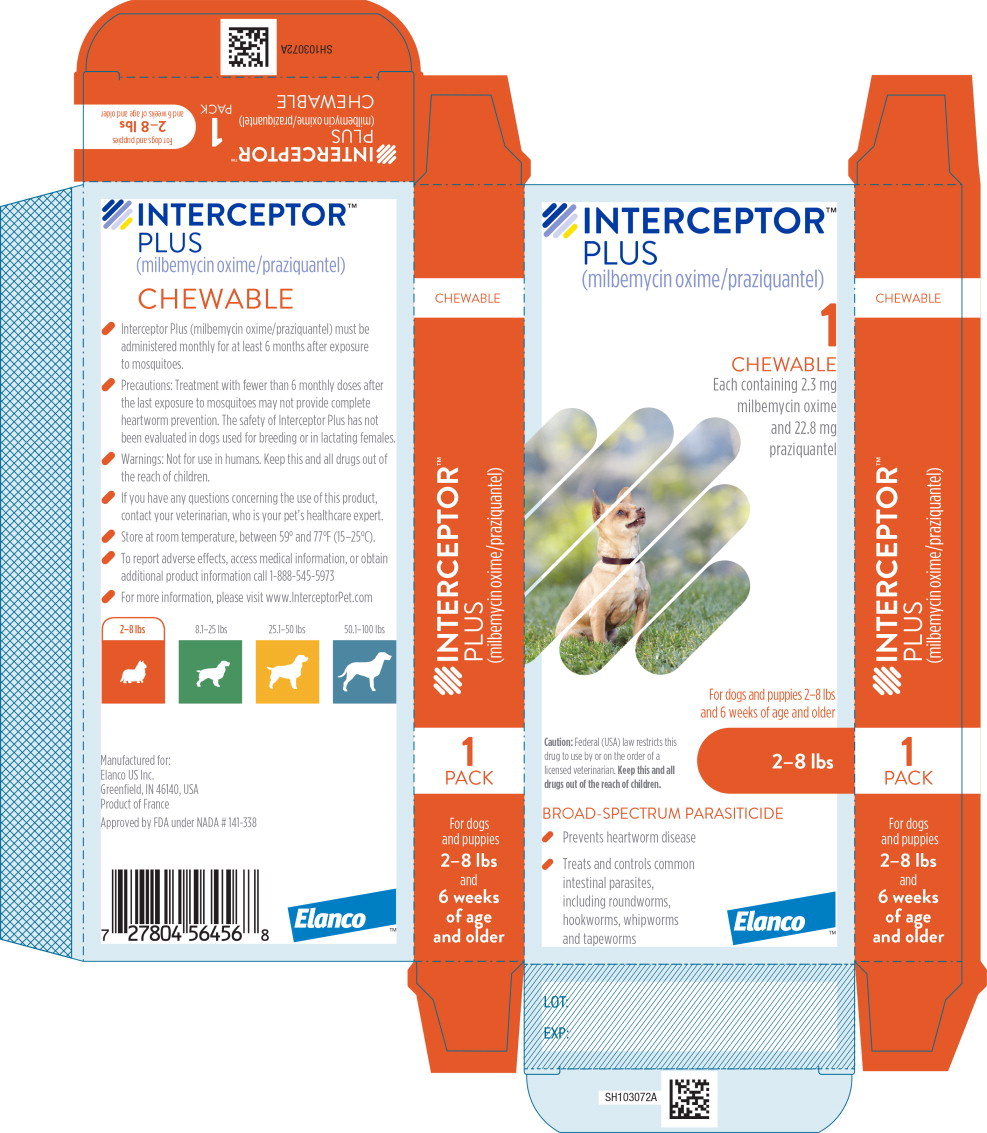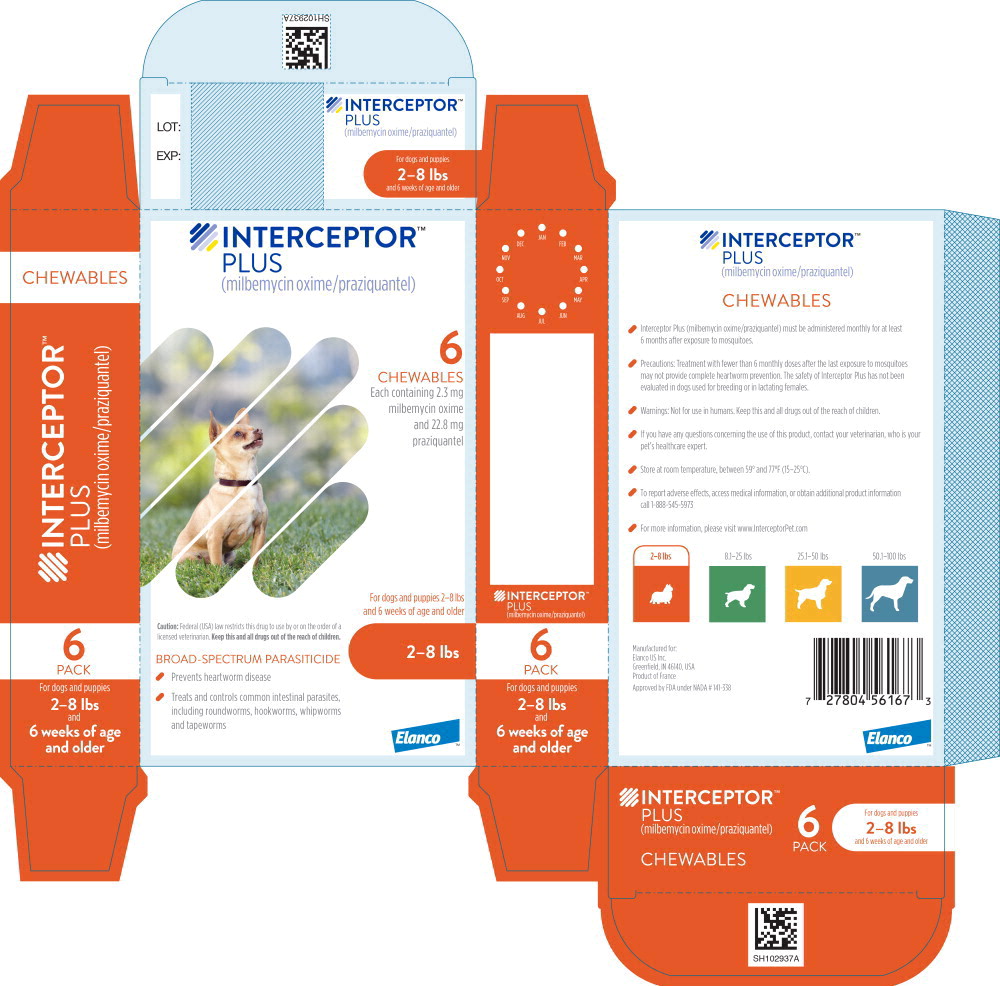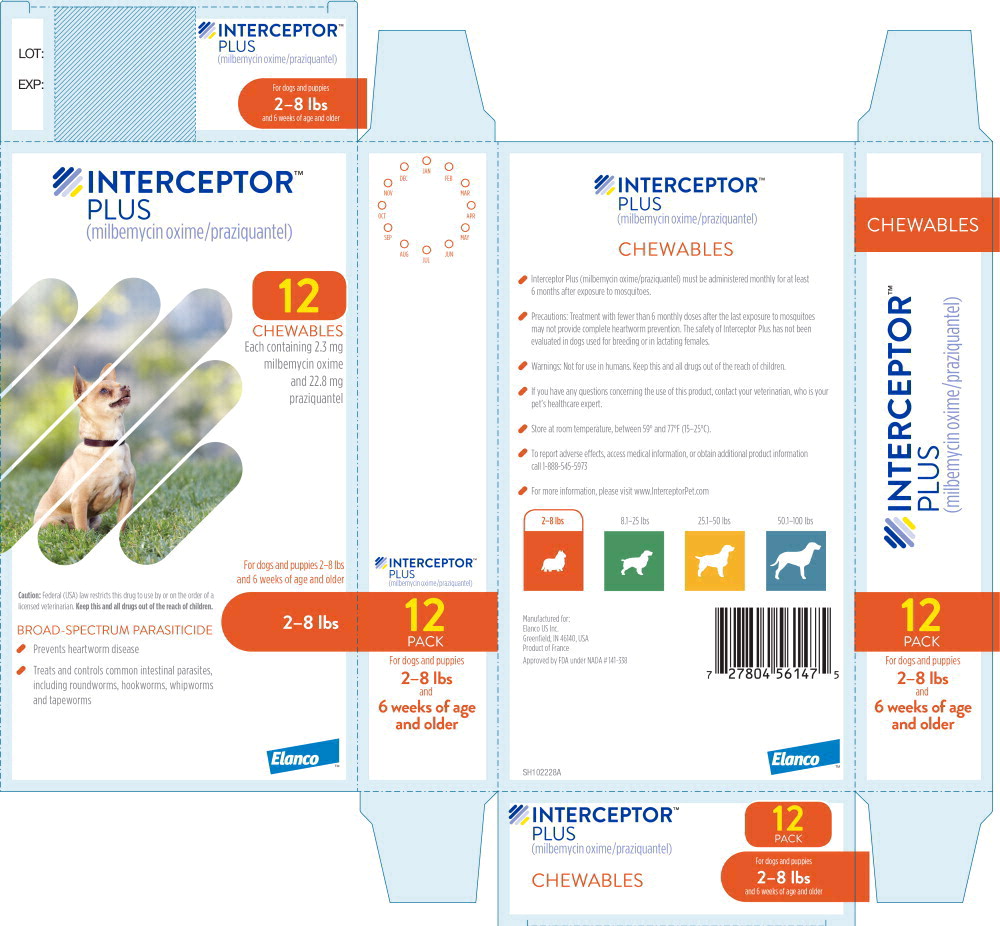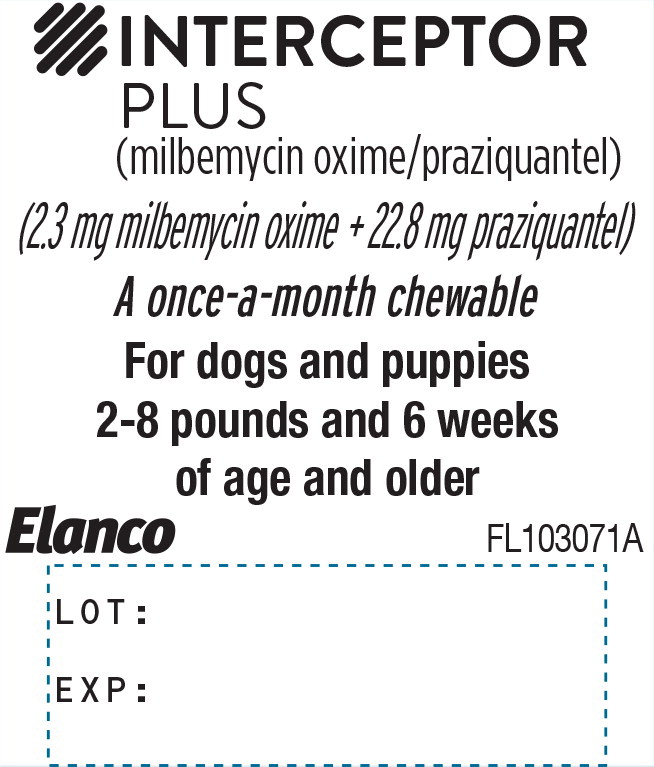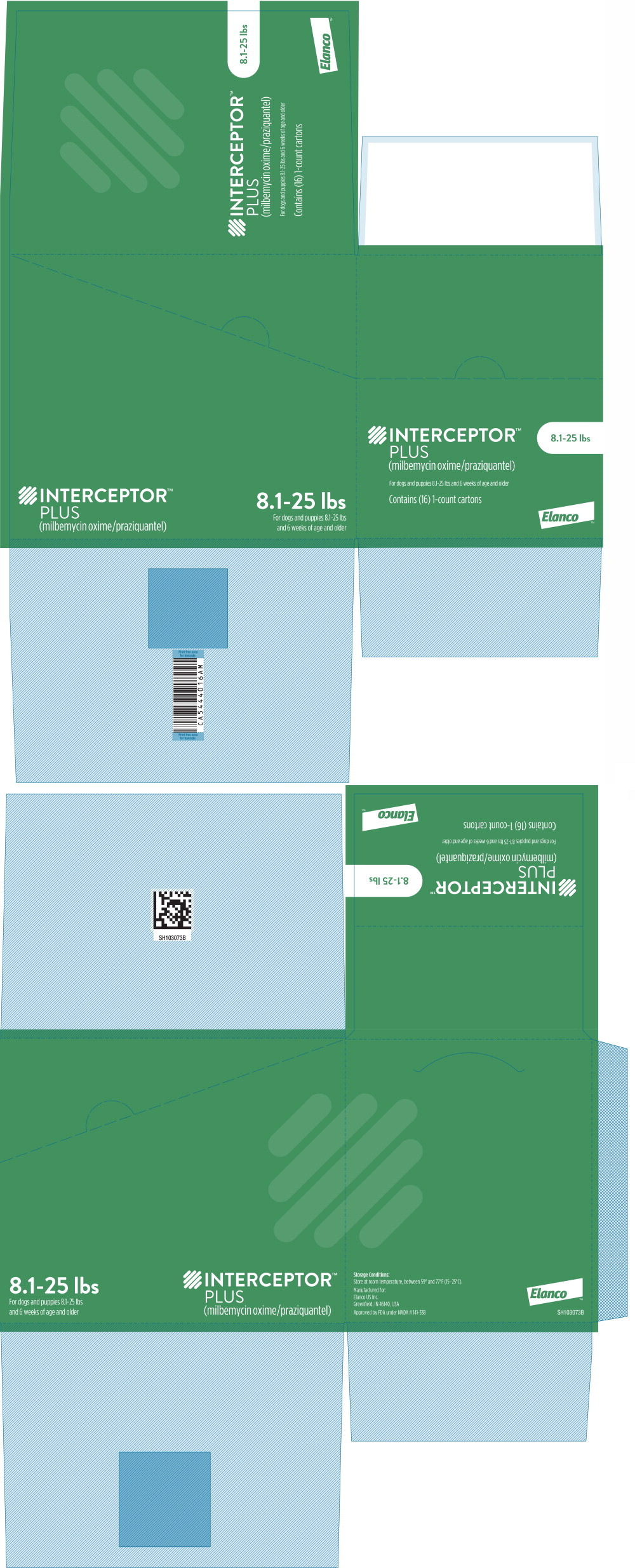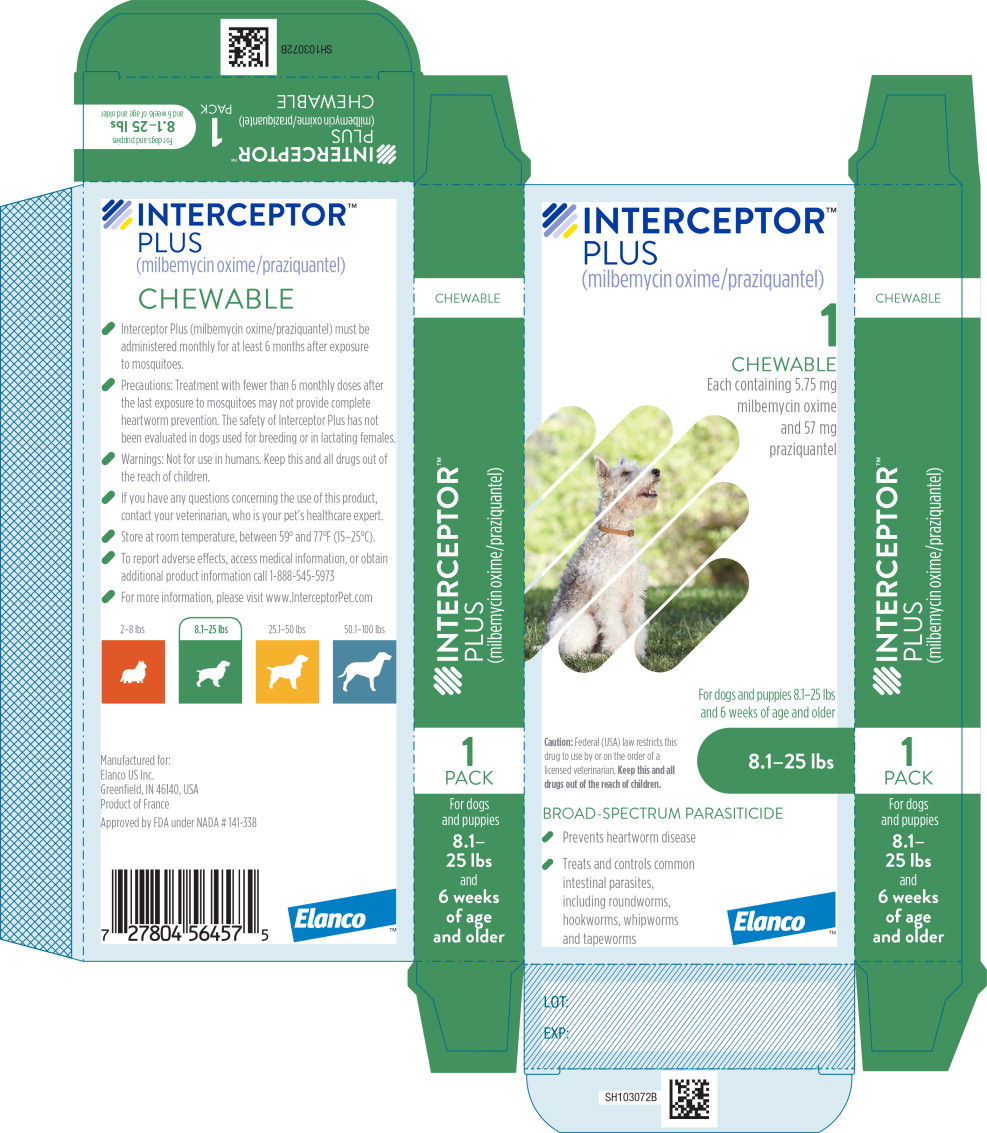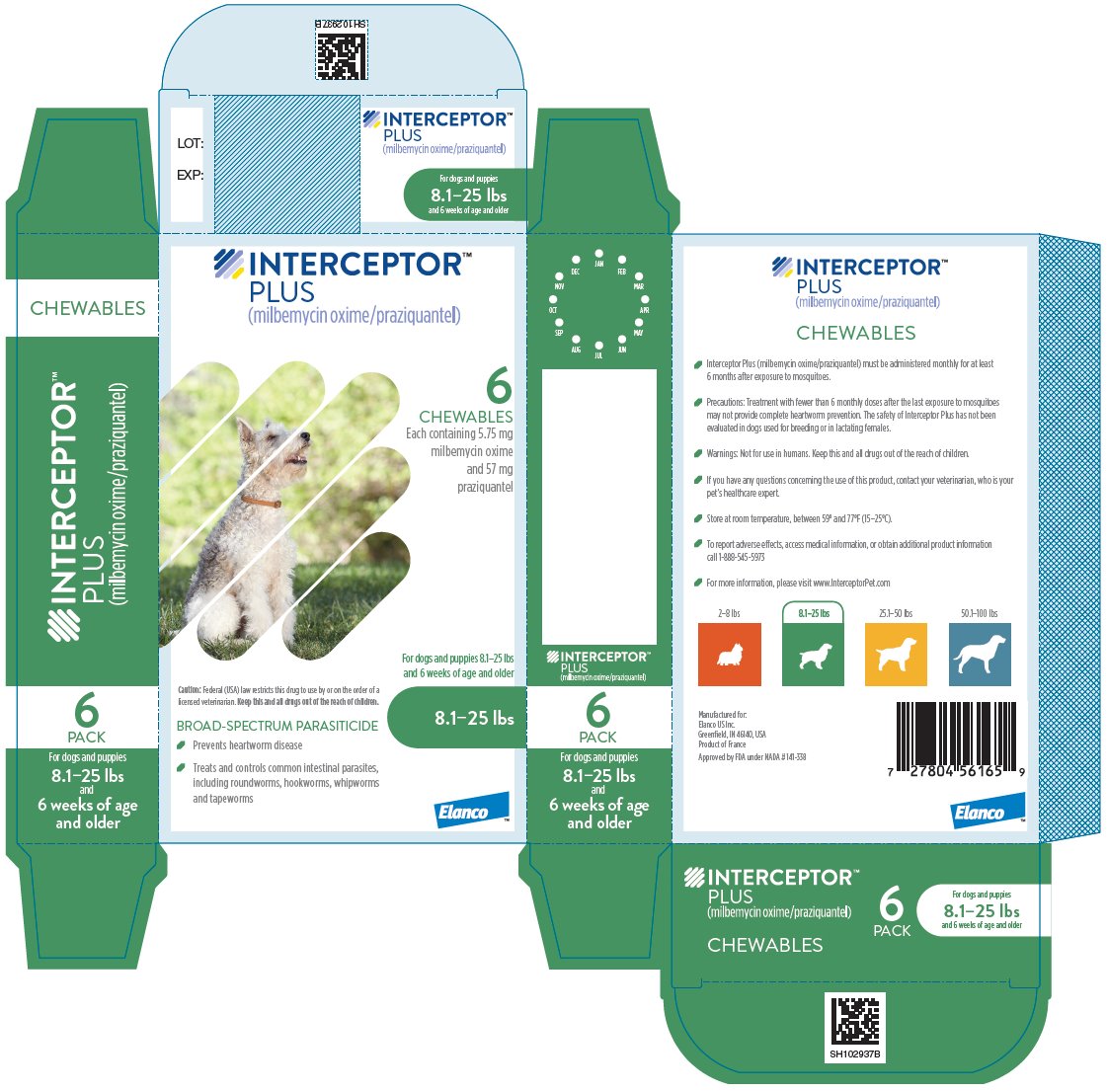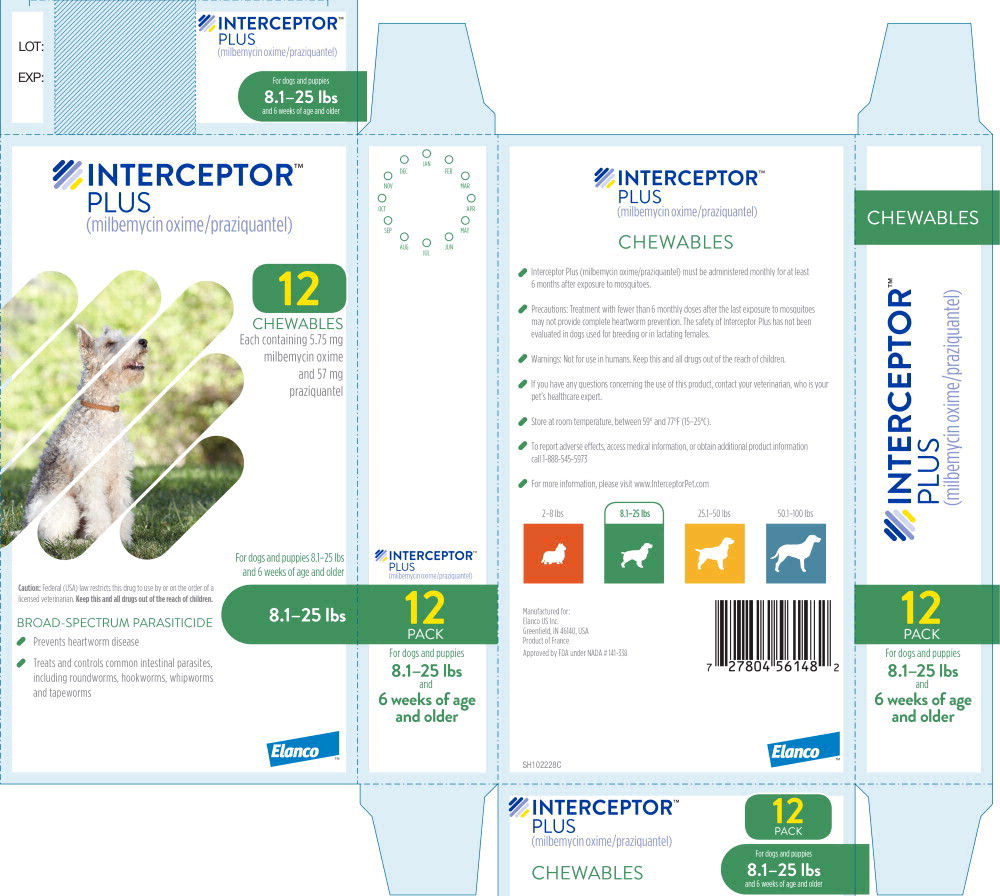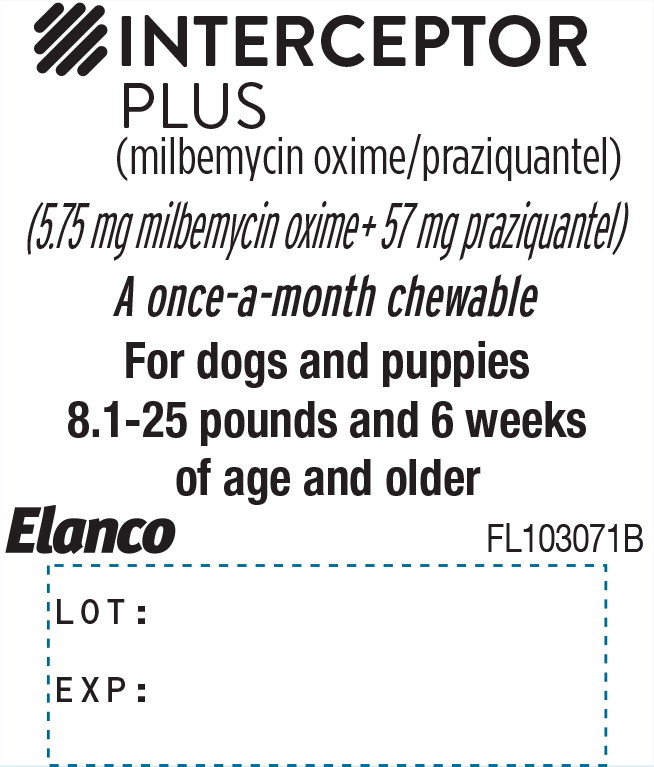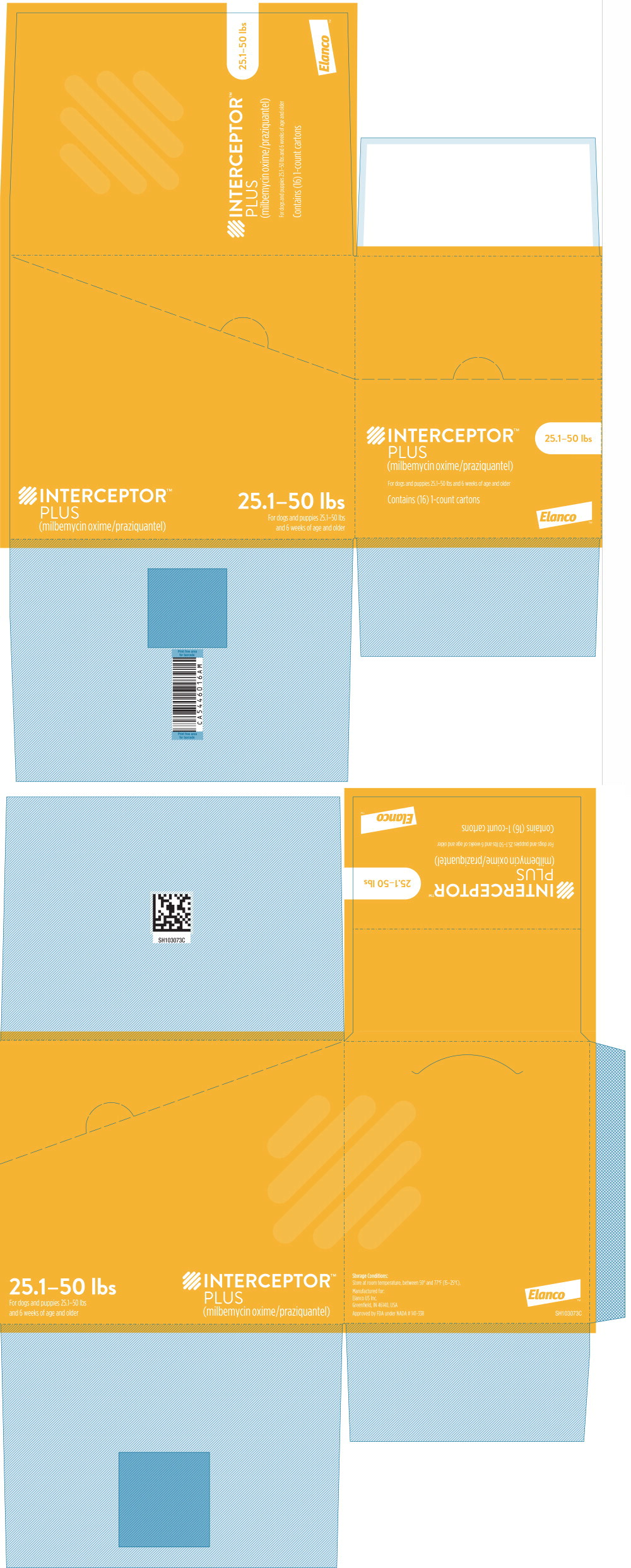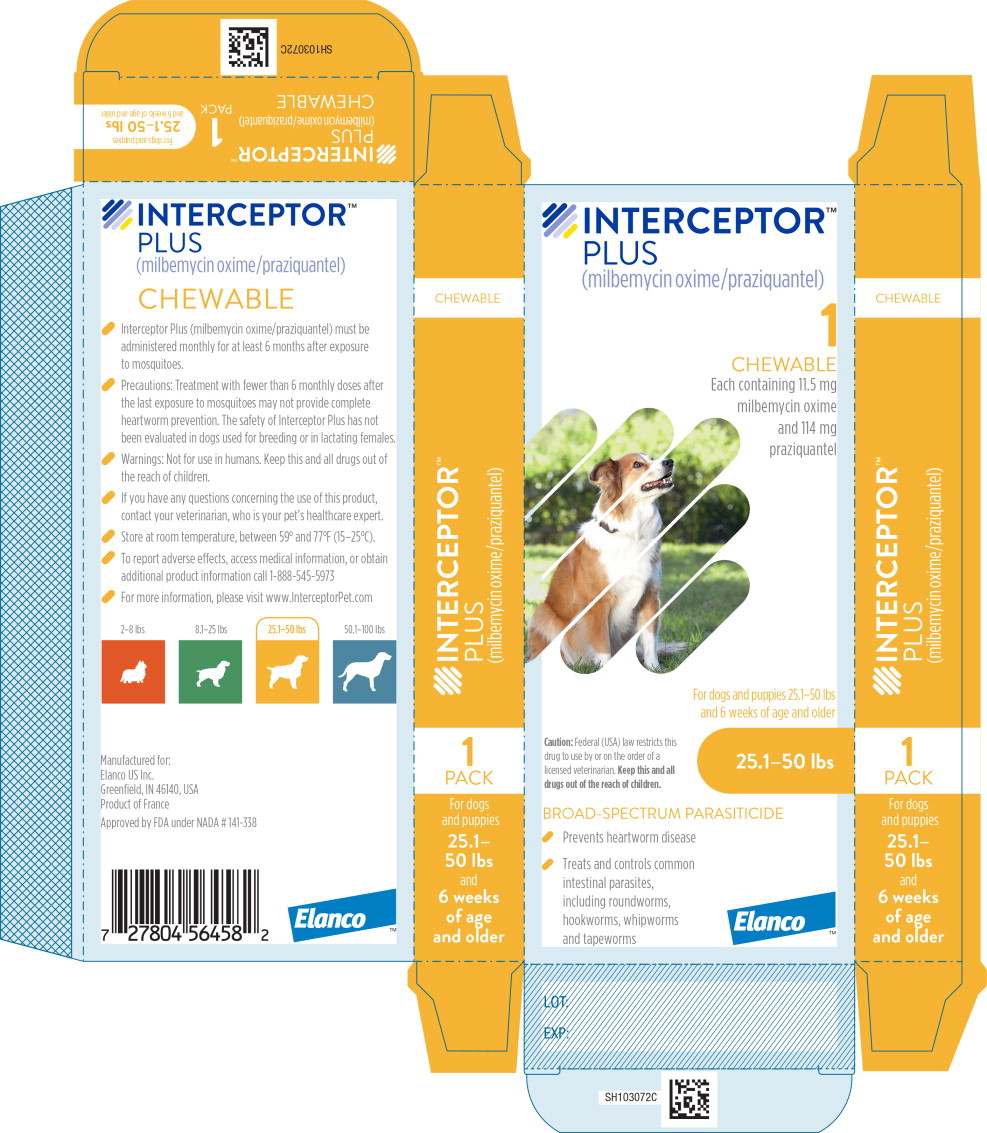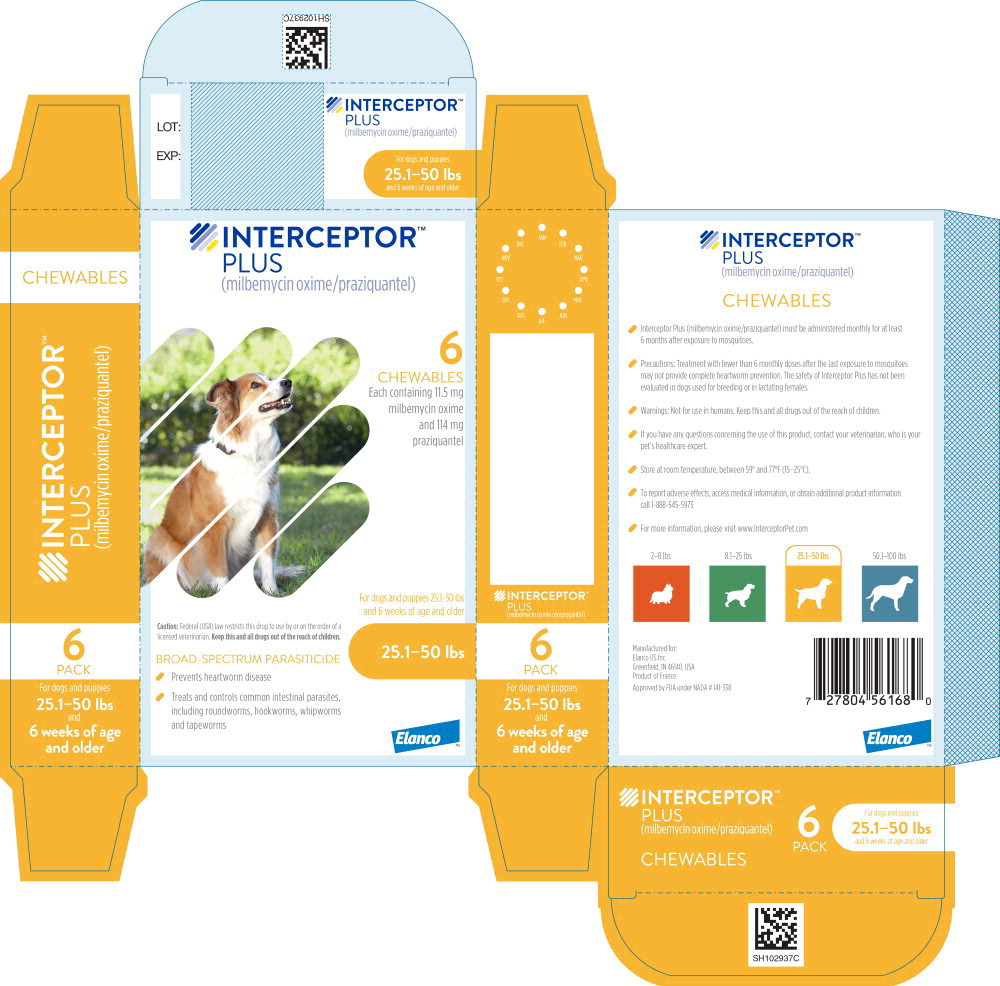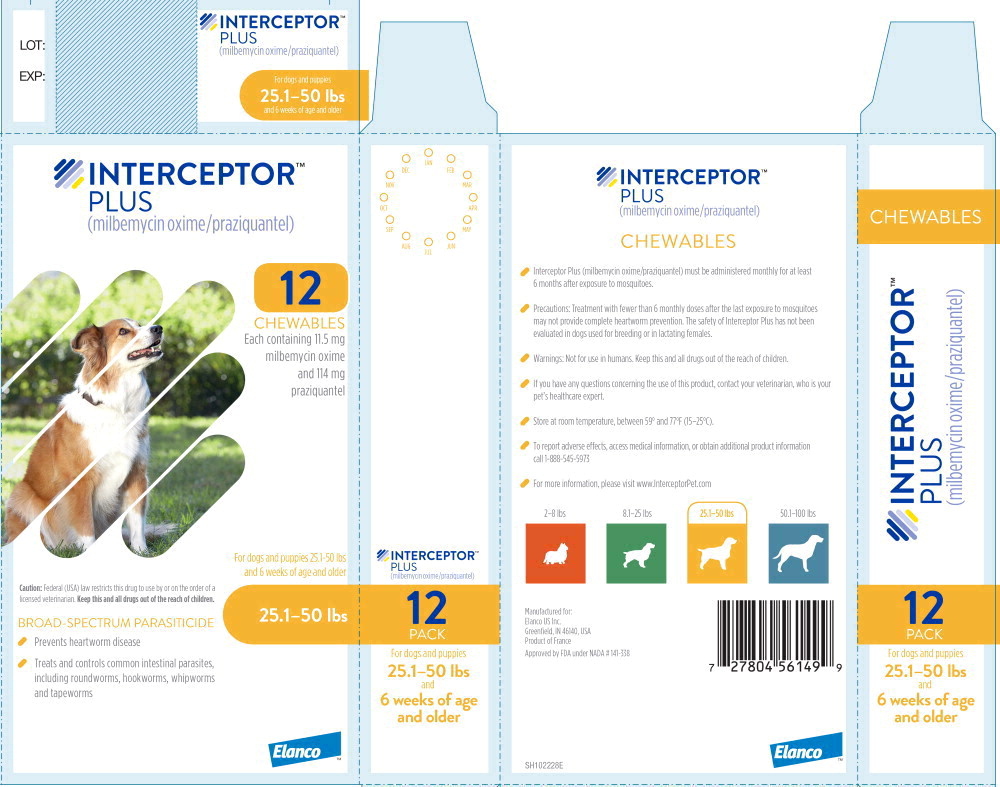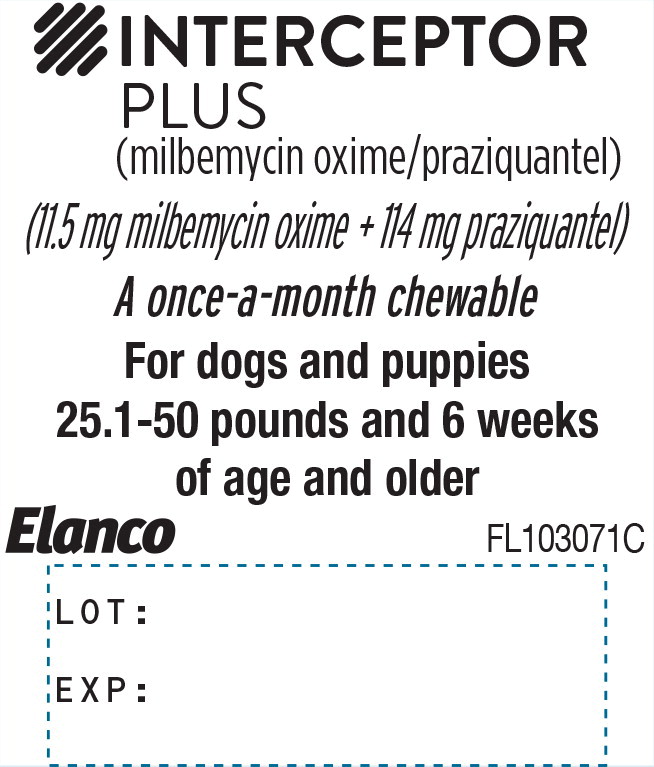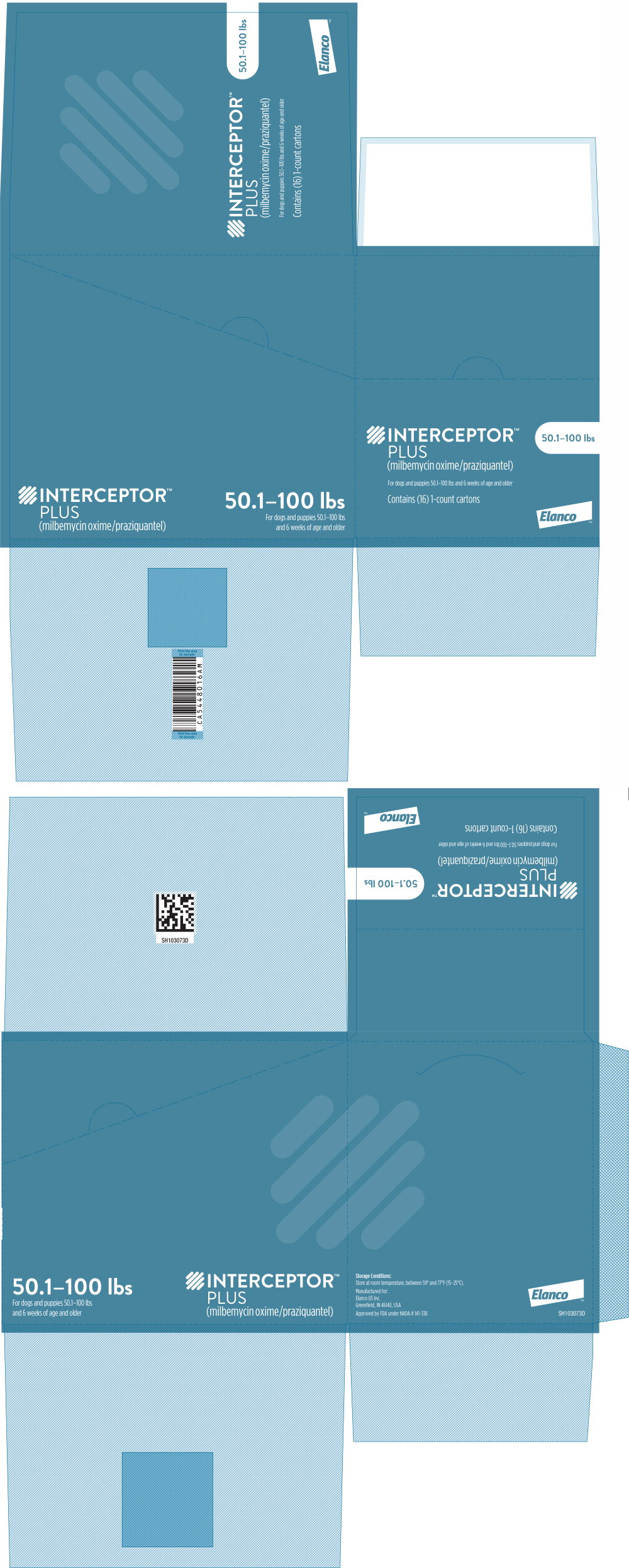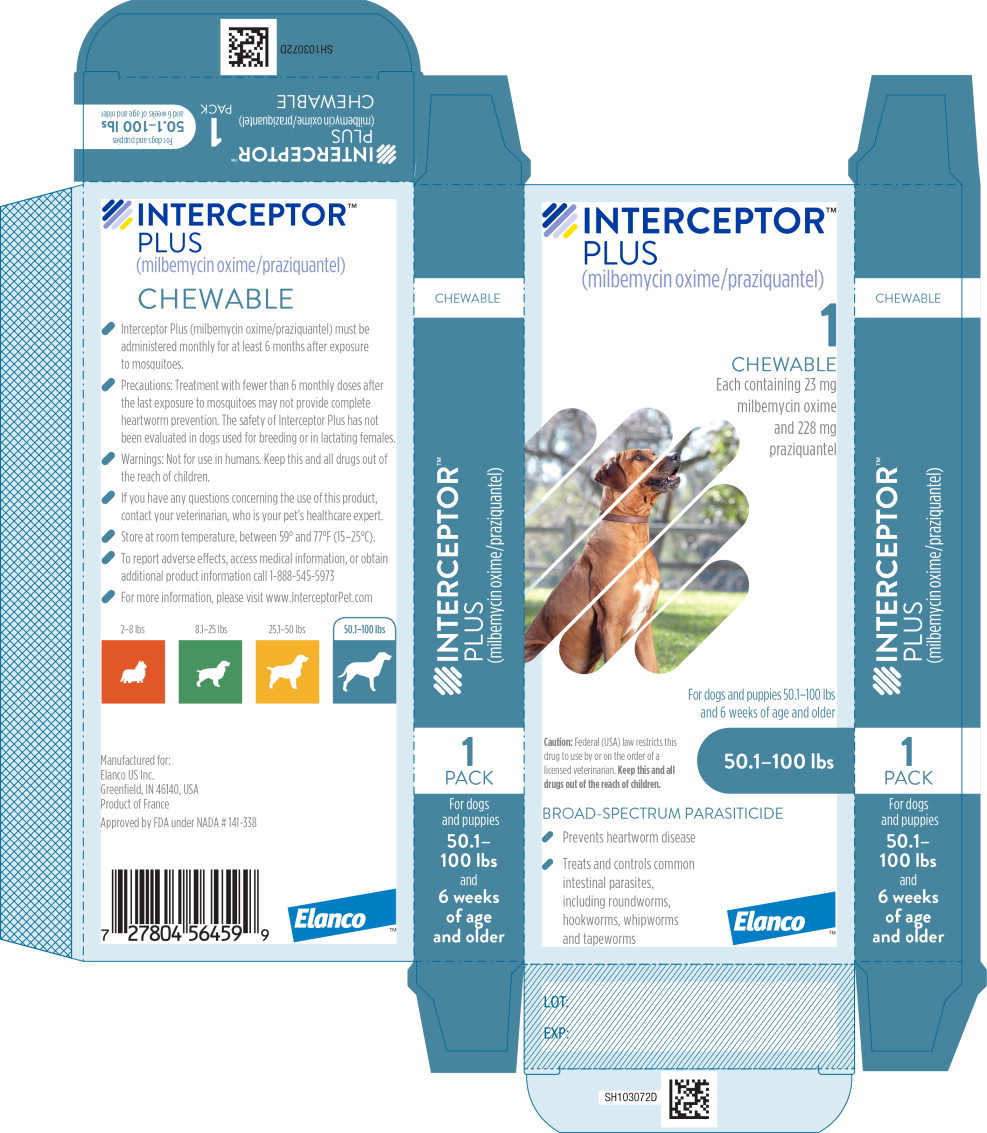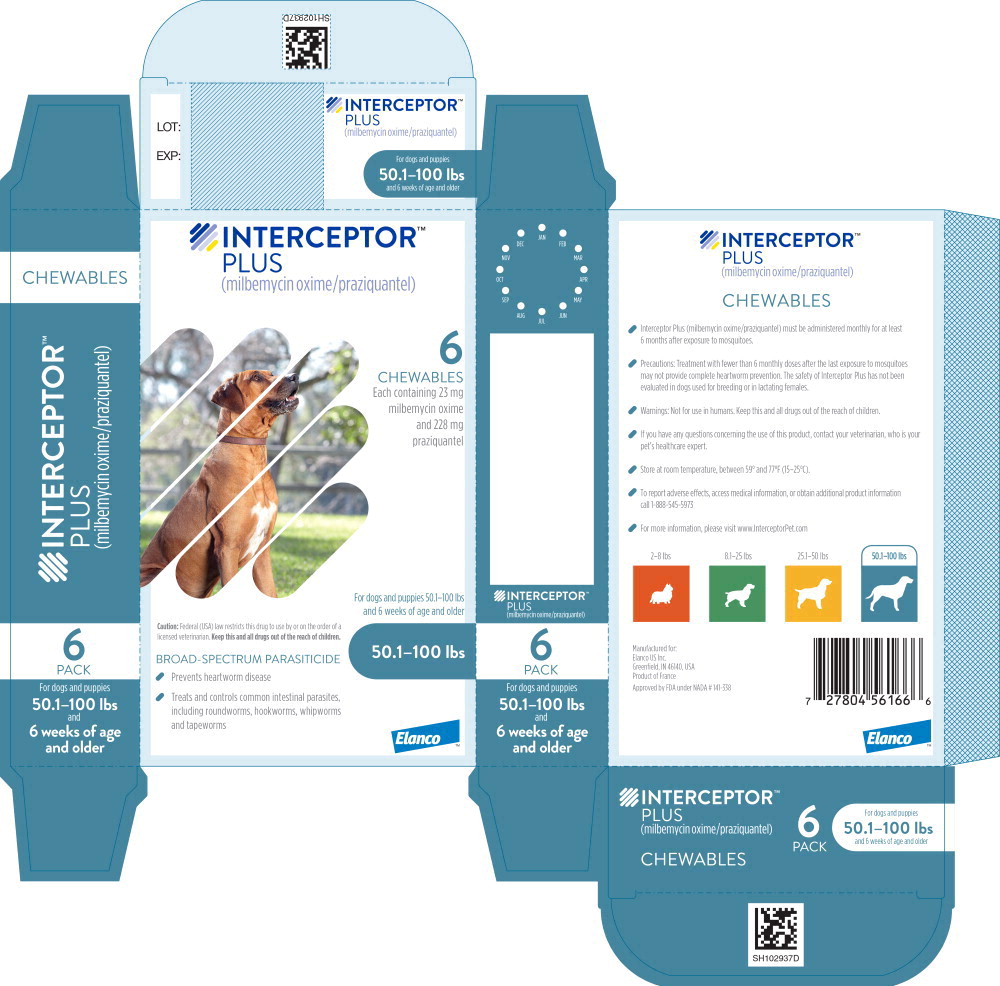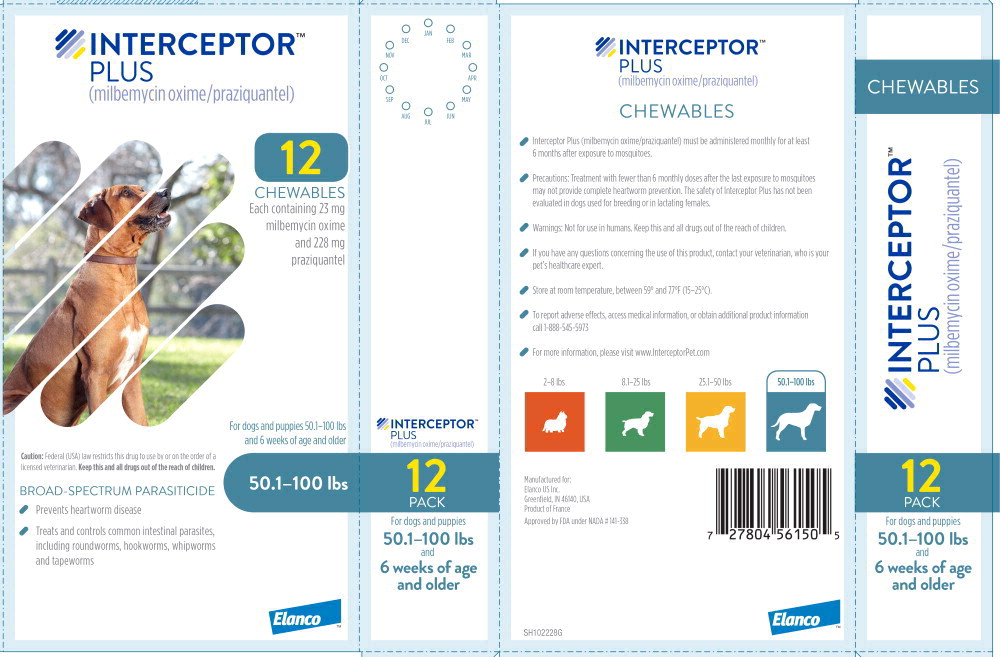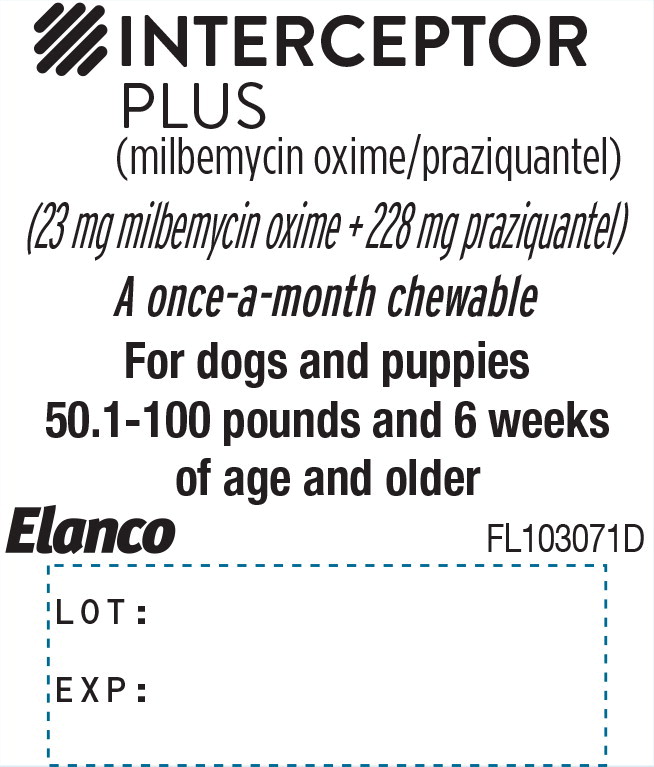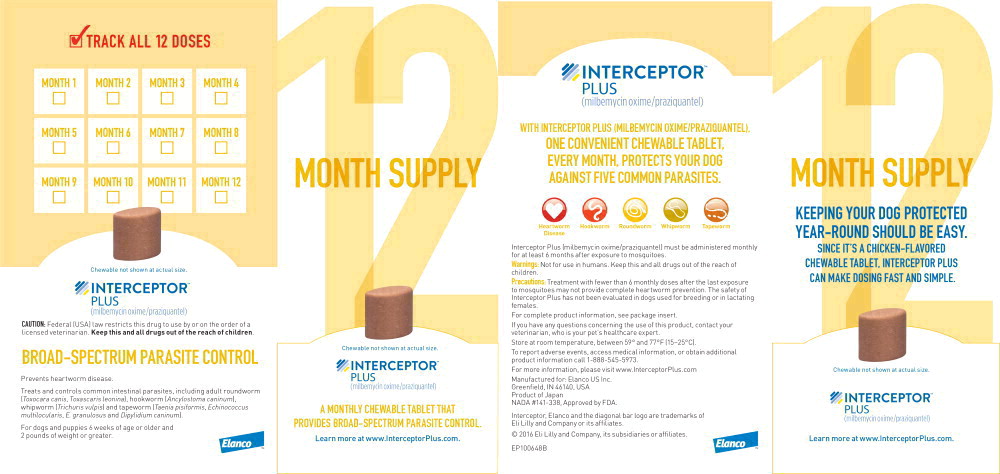 DRUG LABEL: Interceptor Plus
NDC: 58198-5440 | Form: TABLET, CHEWABLE
Manufacturer: Elanco US Inc.
Category: animal | Type: PRESCRIPTION ANIMAL DRUG LABEL
Date: 20240607

ACTIVE INGREDIENTS: milbemycin oxime 2.3 mg/1 1; praziquantel 22.8 mg/1 1

INTERCEPTOR™

PLUS

(milbemycin oxime/praziquantel)

PA103324X

Caution

Federal (USA) law restricts this drug to use by or on the order of a licensed veterinarian.

Description

INTERCEPTOR PLUS is available in four strengths in color-coded packages for oral administration to dogs and puppies according to their weight. Each chewable flavored tablet is formulated to provide a minimum of 0.23 mg/pound (0.5 mg/kg) of milbemycin oxime and 2.28 mg/pound (5 mg/kg) of praziquantel.

Milbemycin oxime consists of the oxime derivatives of 5-didehydromilbemycins in the ratio of approximately 80% A4 (C32H45NO7, MW 555.71) and 20% A3 (C31H43NO7, MW 541.68). Milbemycin oxime is classified as a macrocyclic anthelmintic.

Praziquantel is an isoquinolone anthelmintic with the chemical name 2-(Cyclohexylcarbonyl)-1,2,3,6,7,-11b-hexahydro-4H-pyrazino [2,1-a]isoquinolin-4-one.

Indications

INTERCEPTOR PLUS is indicated for the prevention of heartworm disease caused by Dirofilaria immitis; and for the treatment and control of adult roundworm (Toxocara canis, Toxascaris leonina), adult hookworm (Ancylostoma caninum), adult whipworm (Trichuris vulpis), and adult tapeworm (Taenia pisiformis, Echinococcus multilocularis, Echinococcus granulosus, and Dipylidium caninum) infections in dogs and puppies two pounds of body weight or greater and six weeks of age and older.

Dosage and Administration

INTERCEPTOR PLUS should be administered orally, once every month, at the minimum dosage of 0.23 mg/lb (0.5 mg/kg) milbemycin oxime, and 2.28 mg/lb (5 mg/kg) praziquantel. For heartworm prevention, give once monthly for at least 6 months after exposure to mosquitoes (see EFFECTIVENESS).

Dosage Schedule
Body Weight | Milbemycin Oxime per chewable | Praziquantel per chewable | Number of chewables
2 to 8 lbs. | 2.3 mg | 22.8 mg | One
8.1 to 25 lbs. | 5.75 mg | 57 mg | One
25.1 to 50 lbs. | 11.5 mg | 114 mg | One
50.1 to 100 lbs. | 23 mg | 228 mg | One
Over 100 lbs. | Administer the appropriate combination of chewables.

INTERCEPTOR PLUS may be offered to the dog by hand or added to a small amount of dog food. The chewables should be administered in a manner that encourages the dog to chew, rather than to swallow without chewing. Chewables may be broken into pieces and fed to dogs that normally swallow treats whole. Care should be taken that the dog consumes the complete dose, and treated animals should be observed for a few minutes after administration to ensure that no part of the dose is lost or rejected. If it is suspected that any of the dose has been lost, redosing is recommended.

Heartworm Prevention:

INTERCEPTOR PLUS should be administered at monthly intervals beginning within 1 month of the dog's first seasonal exposure to mosquitoes and continuing until at least 6 months after the dog's last seasonal exposure (see EFFECTIVENESS). INTERCEPTOR PLUS may be administered year-round without interruption. When switching from another heartworm preventative product to INTERCEPTOR PLUS, the first dose of INTERCEPTOR PLUS should be given within a month of the last dose of the former product.

Intestinal Nematode and Cestode Treatment and Control:

Dogs may be exposed to and can become infected with roundworms, whipworms, hookworms, and tapeworms throughout the year, regardless of season or climate. Clients should be advised of appropriate measures to prevent reinfection of their dog with intestinal parasites. Because the prepatent period for E. multilocularis may be as short as 26 days, dogs treated at the labeled monthly intervals may become reinfected and shed eggs between treatments.

Contraindications

There are no known contraindications to the use of INTERCEPTOR PLUS.

Warnings

Not for use in humans. Keep this and all drugs out of the reach of children.

Precautions

Treatment with fewer than 6 monthly doses after the last exposure to mosquitoes may not provide complete heartworm prevention (see EFFECTIVENESS).

Prior to administration of INTERCEPTOR PLUS, dogs should be tested for existing heartworm infections. At the discretion of the veterinarian, infected dogs should be treated to remove adult heartworms. INTERCEPTOR PLUS is not effective against adult D. immitis.

Mild, transient hypersensitivity reactions, such as labored breathing, vomiting, hypersalivation, and lethargy, have been noted in some dogs treated with milbemycin oxime carrying a high number of circulating microfilariae. These reactions are presumably caused by release of protein from dead or dying microfilariae.

Do not use in puppies less than six weeks of age.

Do not use in dogs or puppies less than two pounds of body weight.

The safety of INTERCEPTOR PLUS has not been evaluated in dogs used for breeding or in lactating females. Studies have been performed with milbemycin oxime alone (see ANIMAL SAFETY).

Adverse Reactions

The following adverse reactions have been reported in dogs after administration of milbemycin oxime or praziquantel: vomiting, diarrhea, depression/lethargy, ataxia, anorexia, convulsions, weakness, and salivation.

To report suspected adverse events, for technical assistance or to obtain a copy of the Safety Data Sheet (SDS), contact Elanco US, Inc. at 1-888-545-5973. For additional information about adverse drug experience reporting for animal drugs, contact FDA at 1-888-FDA-VETS or http://www.fda.gov/reportanimalae.

Information for Owner or Person Treating Animal:

Echinococcus multilocularis and Echinococcus granulosus are tapeworms found in wild canids and domestic dogs. E. multilocularis and E. granulosus can infect humans and cause serious disease (alveolar hydatid disease and hydatid disease, respectively).

Owners of dogs living in areas where E. multilocularis or E. granulosus are endemic should be instructed on how to minimize their risk of exposure to these parasites, as well as their dog's risk of exposure. Although INTERCEPTOR PLUS (milbemycine oxime/praziquantel) was 100% effective in laboratory studies in dogs against E. multilocularis and E. granulosus, no studies have been conducted to show that the use of this product will decrease the incidence of alveolar hydatid disease or hydatid disease in humans. Because the prepatent period for E. multilocularis may be as short as 26 days, dogs treated at the labeled monthly intervals may become reinfected and shed eggs between treatments.

Effectiveness

Heartworm Prevention:

In a well-controlled laboratory study, INTERCEPTOR PLUS was 100% effective against induced heartworm infections when administered once monthly for 6 consecutive months. In well-controlled laboratory studies, neither one dose nor two consecutive doses of INTERCEPTOR PLUS provided 100% effectiveness against induced heartworm infections.

Intestinal Nematodes and Cestodes Treatment and Control:

Elimination of the adult stage of hookworm (Ancylostoma caninum), roundworm (Toxocara canis, Toxascaris leonina), whipworm (Trichuris vulpis) and tapeworm (Echinococcus multilocularis, Echinococcus granulosus, Taenia pisiformis and Dipylidium caninum) infections in dogs was demonstrated in well-controlled laboratory studies.

Palatability

In a field study of 115 dogs offered INTERCEPTOR PLUS, 108 dogs (94.0%) accepted the product when offered from the hand as if a treat, 1 dog (0.9%) accepted it from the bowl with food, 2 dogs (1.7%) accepted it when it was placed in the dog's mouth, and 4 dogs (3.5%) refused it.

Animal Safety

INTERCEPTOR PLUS:

In a repeated dose safety study, 40 ten-week-old puppies (10 per group) were dosed with either a sham dose (0X) or 1, 3, or 5X the maximum label exposure of INTERCEPTOR PLUS every 14 days for a total of seven treatments. Ataxia, lethargy, and salivation were seen in the 3X and 5X treated dogs following each of the seven doses. Vomiting was seen in all treatment groups but had a higher incidence in the 3X and 5X treatment groups.

In a repeated dose safety study, 64 six-week-old puppies (16 per group) were dosed with either a sham dose (0X) or 1, 3, or 5X the maximum label exposure of INTERCEPTOR PLUS every 14 days for a total of four treatments. Lethargy was observed in all groups. Ataxia was observed in the three treated groups, including one dog in the 1X treated group. For both lethargy and ataxia the incidence and duration increased in the 3X and 5X groups. These signs were observed during the first 24 hours following treatment. Salivation and tremors were observed in the 3X and 5X treated dogs beginning immediately after dosing and up to six hours post dose. Vomiting was only observed in the 5X treatment group on most, but not all, treatment days.

For INTERCEPTOR PLUS the maximum exposure based on product dosing is 2.5 mg/kg for milbemycin oxime and 25.1 mg/kg for praziquantel, which is higher than the minimum effective dose used in the safety studies for milbemycin oxime (see below).

Milbemycin Oxime:

Two studies were conducted in heartworm-infected dogs treated with milbemycin oxime. Mild, transient hypersensitivity reactions were observed in dogs with high microfilariae counts (see PRECAUTIONS).

Safety studies in pregnant dogs demonstrated that doses of 0.6X the maximum exposure dose of INTERCEPTOR PLUS, (1.5 mg/kg of milbemycin oxime), administered daily from mating through weaning, resulted in measurable concentrations of milbemycin oxime in milk. Puppies nursing these females demonstrated milbemycin oxime-related effects (depression, decreased activity, diarrhea, dehydration, nasal discharge). A subsequent study, which evaluated the daily administration of 0.6X the maximum exposure dose of INTERCEPTOR PLUS, from mating until one week before weaning, demonstrated no effects on the pregnant females or their litters. A study, in which pregnant females were dosed once, at 0.6X the maximum exposure dose of INTERCEPTOR PLUS before, on the day of, or shortly after whelping, resulted in no effects on the puppies.

Some nursing puppies, at 2, 4, and 6 weeks of age, administered oral doses of 9.6 mg/kg milbemycin oxime (3.8X the maximum exposure dose of INTERCEPTOR PLUS) exhibited tremors, vocalization, and ataxia. These effects were all transient and puppies returned to normal within 24 to 48 hours. No effects were observed in puppies administered 0.5 mg/kg milbemycin oxime (minimum label dose).

A rising-dose safety study conducted in rough-coated Collies resulted in ataxia, pyrexia, and periodic recumbency in one of fourteen dogs administered milbemycin oxime at 12.5 mg/kg (5X the maximum exposure dose of INTERCEPTOR PLUS). Prior to receiving the 12.5 mg/kg dose on day 56 of the study, all animals had undergone a dosing regimen consisting of 2.5 mg/kg milbemycin oxime on day 0, followed by 5.0 mg/kg on day 14, and 10.0 mg/kg on day 32. No adverse reactions were observed in any of the Collies treated with doses less than 12.5 mg/kg.

Storage Information

Store at room temperature, between 59° and 77°F (15-25°C).

How Supplied

INTERCEPTOR PLUS is available in four strengths, formulated according to the weight of the dog. Each strength is available in color-coded packages of one, six or twelve chewable tablets each.

Manufactured for: Elanco US Inc.
Greenfield, IN 46140, USA
Approved by FDA under NADA # 141-338

Interceptor, Elanco and the diagonal bar logo are trademarks of Elanco or its affiliates.

© 2021 Elanco or its affiliates

Revision date: April 2021

ElancoTM

Principal Display Panel - Interceptor Plus 2-8 lbs Box Label

2-8 lbs

For dogs and puppies 2-8 lbs
and 6 weeks of age and older

INTERCEPTOR™
PLUS

(milbemycin oxime/praziquantel)

Principal Display Panel - Interceptor Plus 2-8 lbs 1 Chewable Label

INTERCEPTOR™
PLUS

(milbemycin oxime/praziquantel)

1
CHEWABLE
Each containing 2.3 mg
milbemycin oxime
and 22.8 mg
praziquantel

For dogs and puppies 2–8 lbs
and 6 weeks of age and older

2-8 lbs

Caution: Federal (USA) law restricts this
drug to use by or on the order of a
licensed veterinarian. Keep this and all
drugs out of the reach of children.

BROAD-SPECTRUM PARASITICIDE

Prevents heartworm disease

Treats and controls common
intestinal parasites,
including roundworms,
hookworms, whipworms
and tapeworms

Elanco™

Principal Display Panel - Interceptor Plus 2-8 lbs 6 Pack Label

INTERCEPTOR™
PLUS

(milbemycin oxime/praziquantel)

6
CHEWABLES

Each containing 2.3 mg
milbemycin oxime
and 22.8 mg
praziquantel

For dogs and puppies 2-8 lbs
and 6 weeks of age and older

Caution: Federal (USA) law restricts this drug to use by or on the order of a
licensed veterinarian. Keep this and all drugs out of the reach of children.

2-8 lbs

BROAD-SPECTRUM PARASITICIDE

Prevents heartworm disease

Treats and controls common intestinal parasites,
including roundworms, hookworms, whipworms
and tapeworms

Elanco™

Principal Display Panel - Interceptor Plus 2-8 lbs 12 Pack Label

INTERCEPTOR™
PLUS

(milbemycin oxime/praziquantel)

12

CHEWABLES

Each containing 2.3 mg
milbemycin oxime
and 22.8 mg
praziquantel

For dogs and puppies 2-8 lbs
and 6 weeks of age and older

Caution: Federal (USA) law restricts this drug to use by or on the order of a
licensed veterinarian. Keep this and all drugs out of the reach of children.

2-8 lbs

BROAD-SPECTRUM PARASITICIDE

Prevents heartworm disease

Treats and controls common intestinal parasites,
including roundworms, hookworms, whipworms
and tapeworms

Elanco™

Principal Display Panel - Interceptor Plus 2-8 lbs Blister Label

INTERCEPTOR
PLUS

(milbemycin oxime/praziquantel)

(2.3 mg milbemycin oxime+ 22.8 mg praziquantel)

A once-a-month chewable

For dogs and puppies
2-8 pounds and 6 weeks
of age and older

Elanco

FL103071A

LOT:

EXP:

Principal Display Panel - Interceptor Plus 8.1-25 lbs Box Label

8.1-25 lbs

For dogs and puppies 8.1–25 lbs
and 6 weeks of age and older

INTERCEPTOR™
PLUS

(milbemycin oxime/praziquantel)

Principal Display Panel - Interceptor Plus 8.1-25 lbs 1 Chewable Label

INTERCEPTOR™
PLUS

(milbemycin oxime/praziquantel)

1
CHEWABLE
Each containing 5.75 mg
milbemycin oxime
and 57 mg
praziquantel

For dogs and puppies 8.1-25 lbs
and 6 weeks of age and older

8.1-25 lbs

Caution: Federal (USA) law restricts this
drug to use by or on the order of a
licensed veterinarian. Keep this and all
drugs out of the reach of children.

BROAD-SPECTRUM PARASITICIDE

Prevents heartworm disease

Treats and controls common
intestinal parasites,
including roundworms,
hookworms, whipworms
and tapeworms

Elanco™

Principal Display Panel - Interceptor Plus 8.1-25 lbs 6 Pack Label

INTERCEPTOR™
PLUS

(milbemycin oxime/praziquantel)

6
CHEWABLES

Each containing 5.75 mg
milbemycin oxime
and 57 mg
praziquantel

For dogs and puppies 8.1-25 lbs
and 6 weeks of age and older

Caution: Federal (USA) law restricts this drug to use by or on the order of a
licensed veterinarian. Keep this and all drugs out of the reach of children.

8.1-25 lbs

BROAD-SPECTRUM PARASITICIDE

Prevents heartworm disease

Treats and controls common intestinal parasites,
including roundworms, hookworms, whipworms
and tapeworms

Elanco™

Principal Display Panel - Interceptor Plus 8.1-25 lbs 12 Pack Label

INTERCEPTOR™
PLUS

(milbemycin oxime/praziquantel)

12
CHEWABLES

Each containing 5.75 mg
milbemycin oxime
and 57 mg
praziquantel

For dogs and puppies 8.1-25 lbs
and 6 weeks of age and older

Caution: Federal (USA) law restricts this drug to use by or on the order of a
licensed veterinarian. Keep this and all drugs out of the reach of children.

8.1-25 lbs

BROAD-SPECTRUM PARASITICIDE

Prevents heartworm disease

Treats and controls common intestinal parasites,
including roundworms, hookworms, whipworms
and tapeworms

Elanco™

Principal Display Panel - Interceptor Plus 8.1-25 lbs Blister Label

INTERCEPTOR
PLUS

(milbemycin oxime/praziquantel)

(5.75 mg milbemycin oxime+ 57 mg praziquantel)

A once-a-month chewable

For dogs and puppies
8.1-25 pounds and 6 weeks
of age and older

Elanco

FL103071B

LOT:

EXP:

Principal Display Panel - Interceptor Plus 25.1-50 lbs Box Label

25.1-50 lbs

For dogs and puppies 25.1-50 lbs
and 6 weeks of age and older

INTERCEPTOR™
PLUS

(milbemycin oxime/praziquantel)

Principal Display Panel - Interceptor Plus 25.1-50 lbs 1 Pack Label

INTERCEPTOR™
PLUS

(milbemycin oxime/praziquantel)

1
CHEWABLE

Each containing 11.5 mg
milbemycin oxime
and 114 mg
praziquantel

For dogs and puppies 25.1-50 lbs
and 6 weeks of age and older

Caution: Federal (USA) law restricts this
drug to use by or on the order of a
licensed veterinarian. Keep this and all
drugs out of the reach of children.

25.1-50 lbs

BROAD-SPECTRUM PARASITICIDE

Prevents heartworm disease

Treats and controls common
intestinal parasites,
including roundworms,
hookworms, whipworms
and tapeworms

Elanco™

Principal Display Panel - Interceptor Plus 25.1-50 lbs 6 Pack Label

INTERCEPTOR™
PLUS

(milbemycin oxime/praziquantel)

6
CHEWABLES

Each containing 11.5 mg
milbemycin oxime
and 114 mg
praziquantel

For dogs and puppies 25.1-50 lbs
and 6 weeks of age and older

Caution: Federal (USA) law restricts this drug to use by or on the order of a
licensed veterinarian. Keep this and all drugs out of the reach of children.

25.1-50 lbs

BROAD-SPECTRUM PARASITICIDE

Prevents heartworm disease

Treats and controls common intestinal parasites,
including roundworms, hookworms, whipworms
and tapeworms

Elanco™

Principal Display Panel - Interceptor Plus 25.1-50 lbs 12 Pack Label

INTERCEPTOR™
PLUS

(milbemycin oxime/praziquantel)

12
CHEWABLES

Each containing 11.5 mg
milbemycin oxime
and 114 mg
praziquantel

For dogs and puppies 25.1-50 lbs
and 6 weeks of age and older

Caution: Federal (USA) law restricts this drug to use by or on the order of a
licensed veterinarian. Keep this and all drugs out of the reach of children.

25.1-50 lbs

BROAD-SPECTRUM PARASITICIDE

Prevents heartworm disease

Treats and controls common intestinal parasites,
including roundworms, hookworms, whipworms
and tapeworms

Elanco™

Principal Display Panel - Interceptor Plus 25.1-50 lbs Blister Label

INTERCEPTOR
PLUS

(milbemycin oxime/praziquantel)

(11.5 mg milbemycin oxime+ 114 mg praziquantel)

A once-a-month chewable

For dogs and puppies
25.1-50 pounds and 6 weeks
of age and older

Elanco

FL103071C

LOT:

EXP:

Principal Display Panel - Interceptor Plus 50.1-100 lbs Box Label

50.1-100 lbs

For dogs and puppies 50.1-100 lbs
and 6 weeks of age and older

INTERCEPTOR™
PLUS

(milbemycin oxime/praziquantel)

Principal Display Panel - Interceptor Plus 50.1-100 lbs 1 Pack Label

INTERCEPTOR™
PLUS

(milbemycin oxime/praziquantel)

1
CHEWABLE

Each containing 23 mg
milbemycin oxime
and 228 mg
praziquantel

For dogs and puppies 50.1-100 lbs
and 6 weeks of age and older

Caution: Federal (USA) law restricts this
drug to use by or on the order of a
licensed veterinarian. Keep this and all
drugs out of the reach of children.

50.1-100 lbs

BROAD-SPECTRUM PARASITICIDE

Prevents heartworm disease

Treats and controls common intestinal parasites,
including roundworms, hookworms, whipworms
and tapeworms

Elanco™

Principal Display Panel - Interceptor Plus 50.1-100 lbs 6 Pack Label

INTERCEPTOR™
PLUS

(milbemycin oxime/praziquantel)

6
CHEWABLES

Each containing 23 mg
milbemycin oxime
and 228 mg
praziquantel

For dogs and puppies 50.1-100 lbs
and 6 weeks of age and older

Caution: Federal (USA) law restricts this drug to use by or on the order of a
licensed veterinarian. Keep this and all drugs out of the reach of children.

50.1-100 lbs

BROAD-SPECTRUM PARASITICIDE

Prevents heartworm disease

Treats and controls common intestinal parasites,
including roundworms, hookworms, whipworms
and tapeworms

Elanco™

Principal Display Panel - Interceptor Plus 50.1-100 lbs 12 Pack Label

INTERCEPTOR™
PLUS

(milbemycin oxime/praziquantel)

12
CHEWABLES

Each containing 23 mg
milbemycin oxime
and 228 mg
praziquantel

For dogs and puppies 50.1-100 lbs
and 6 weeks of age and older

Caution: Federal (USA) law restricts this drug to use by or on the order of a
licensed veterinarian. Keep this and all drugs out of the reach of children.

50.1-100 lbs

BROAD-SPECTRUM PARASITICIDE

Prevents heartworm disease

Treats and controls common intestinal parasites,
including roundworms, hookworms, whipworms
and tapeworms

Elanco™

Principal Display Panel - Interceptor Plus 50.1-100 lbs Blister Label

INTERCEPTOR™
PLUS

(milbemycin oxime/praziquantel)

(23 mg milbemycin oxime+ 228 mg praziquantel)

A once-a-month chewable

For dogs and puppies
50.1-100 pounds and 6 weeks
of age and older

Elanco

FL103071D

Principal Display Panel - 12 Month Supply Label

INTERCEPTOR™
PLUS

(milbemycin oxime/praziquantel)

WITH INTERCEPTOR PLUS (MILBEMYCIN OXIME/PRAZIQUANTEL),
ONE CONVENIENT CHEWABLE TABLET,
EVERY MONTH, PROTECTS YOUR DOG
AGAINST FIVE COMMON PARASITES.

Heartworm
Disease

Hookworm

Roundworm

Whipworm

Tapeworm